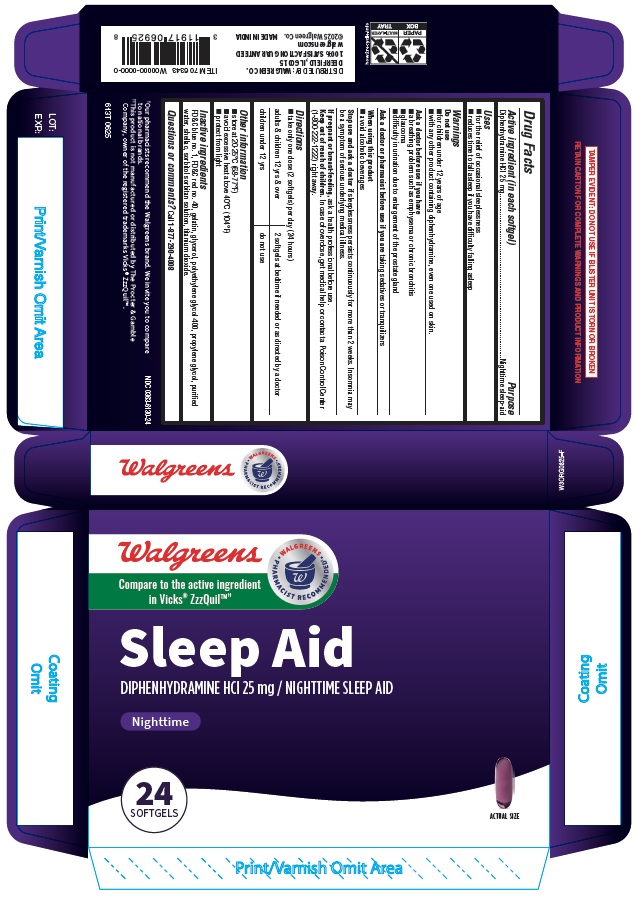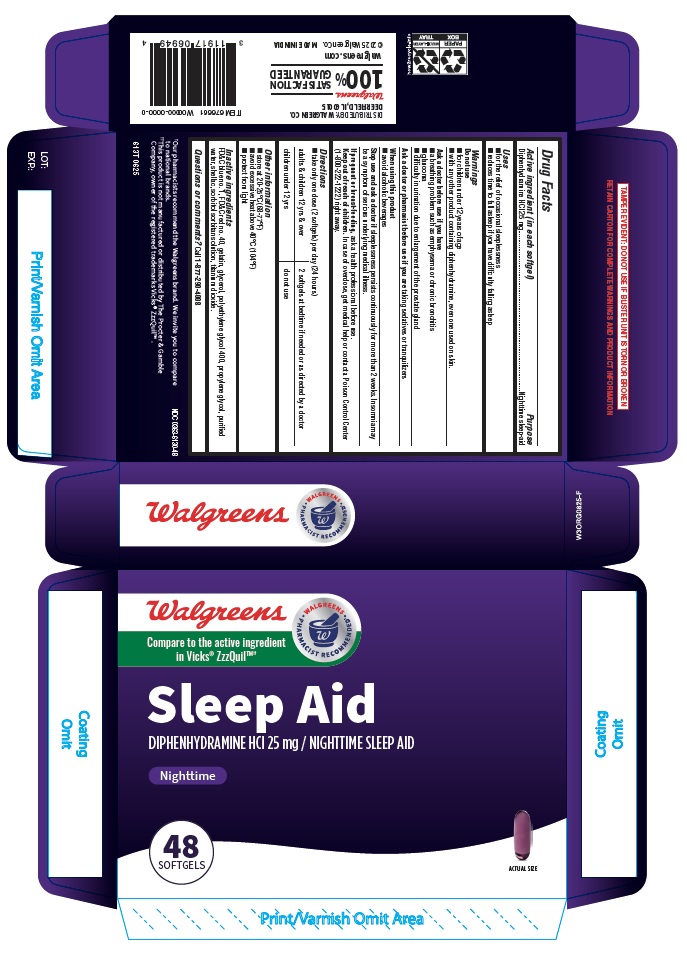 DRUG LABEL: Sleep Aid
NDC: 0363-6130 | Form: CAPSULE
Manufacturer: WALGREENS
Category: otc | Type: HUMAN OTC DRUG LABEL
Date: 20250904

ACTIVE INGREDIENTS: DIPHENHYDRAMINE HYDROCHLORIDE 25 mg/1 1
INACTIVE INGREDIENTS: FD&C RED NO. 40; SHELLAC; FD&C BLUE NO. 1; GELATIN, UNSPECIFIED; WATER; TITANIUM DIOXIDE; PROPYLENE GLYCOL; SORBITAN; SORBITOL SOLUTION; GLYCERIN; POLYETHYLENE GLYCOL 400

Walgreens 613T Diphenhydramine HCl 25mg capsule

Drug Facts

Active ingredient (in each softgel)

Diphenhydramine HCl 25 mg

Purpose

Nighttime sleep-aid

Uses

- for the relief of occasional sleeplessness
- reduces time to fall asleep if you have difficulty falling asleep

Warnings

Do not use

- for children under 12 years of age
- with any other product containing diphenhydramine, even one used on skin.

Ask a doctor before use if you have

- a breathing problem such as emphysema or chronic bronchitis
- glaucoma
- difficulty in urination due to enlargement of the prostate gland

Ask a doctor or pharmacist before use if you are taking sedatives or tranquilizers

When using this product

- avoid alcoholic beverages

Stop use and ask a doctor if sleeplessness persists continuously for more than 2 weeks. Insomnia may be a symptom of serious underlying medical illness.

PREGNANCY OR BREAST FEEDING

If pregnant or breast-feeding, ask a health professional before use.

Keep out of reach of children. In case of overdose, get medical help or contact a Poison Control Center (1-800-222-1222) right away.

Directions

- take only one dose (2 softgels) per day (24 hours)

adults & children 12 yrs & over | 2 softgels at bedtime if needed or as directed by a doctor
children under 12 yrs | do not use

Other information

- store at 20-25° C (68-77°F)
- avoid excessive heat above 40°C (104°F)
- protect from light.

Inactive ingredients

FD&C blue no. 1, FD&C red no. 40, gelatin, glycerol, polyethylene glycol 400, propylene glycol, purified water, shellac, sorbitol sorbitan solution, titanium dioxide.

Questions or comments? Call 1-877-290-4008